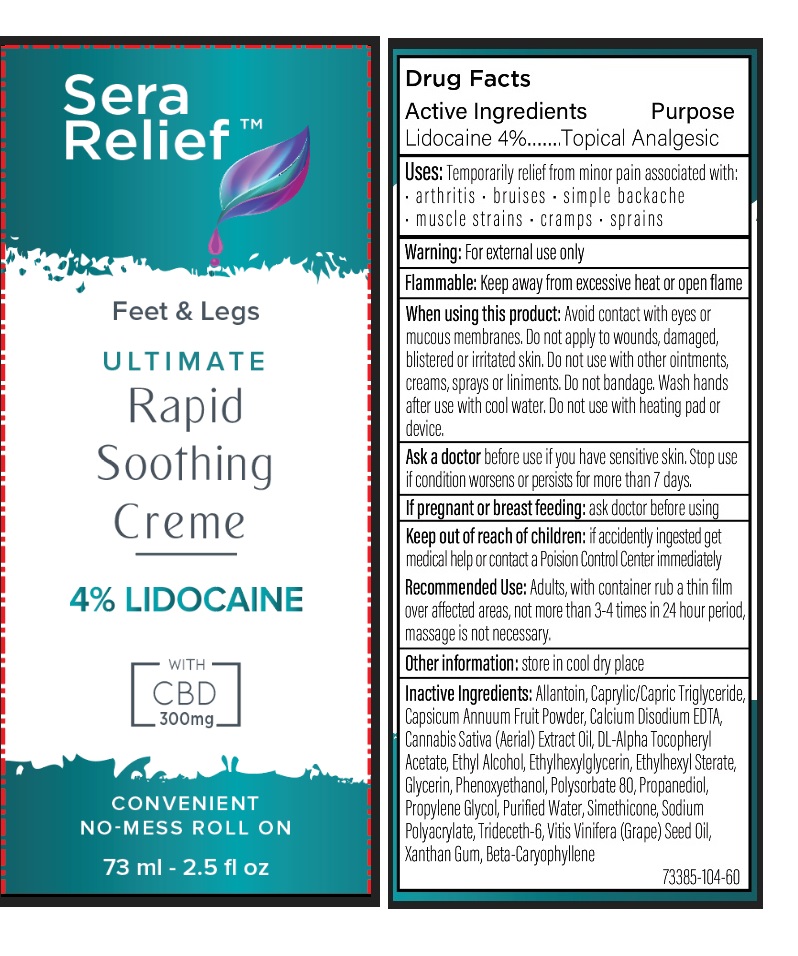 DRUG LABEL: SERA RELIEF ULTIMATE RAPID SOOTHING CREME
NDC: 73385-104 | Form: CREAM
Manufacturer: Sera Labs, Inc., The
Category: otc | Type: HUMAN OTC DRUG LABEL
Date: 20191025

ACTIVE INGREDIENTS: LIDOCAINE HYDROCHLORIDE 4 g/100 mL
INACTIVE INGREDIENTS: ALLANTOIN; MEDIUM-CHAIN TRIGLYCERIDES; PAPRIKA; EDETATE CALCIUM DISODIUM ANHYDROUS; CANNABIS SATIVA SUBSP. SATIVA FLOWERING TOP; .ALPHA.-TOCOPHEROL ACETATE, DL-; ALCOHOL; ETHYLHEXYLGLYCERIN; ETHYLHEXYL STEARATE; GLYCERIN; PHENOXYETHANOL; POLYSORBATE 80; PROPANEDIOL; PROPYLENE GLYCOL; WATER; DIMETHICONE; SODIUM POLYACRYLATE (2500000 MW); TRIDECETH-6; GRAPE SEED OIL; XANTHAN GUM; CARYOPHYLLENE

SERA RELIEF ULTIMATE RAPID SOOTHING CREME

Active Ingredients

Lidocaine 4%

Purpose

Topical Analgesic

INDICATIONS AND USAGE

Uses: Temporarily relief from minor pain associated with: • arthritis • bruises • simple backache • muscle strains • cramps • sprains

WARNINGS

Warning: For external use only
Flammable: Keep away from excessive heat or open flame

When using this product: Avoid contact with eyes or mucous membrane. Do not apply to wounds, damaged, blistered or irritated skin. Do not use with other ointments, creams, sprays or liniments. Do not bandage. Wash hands after use with cool water. Do not use with heating pad or device.

Ask a doctor before use if you have sensitive skin. Stop use if condition worsens or persists for more than 7 days.

If pregnant or breast feeding: ask doctor before using

Keep out of reach of children: if accidentally ingested get medical help or contact a Poison Control Center immediately

DOSAGE AND ADMINISTRATION

Recommended Use: Adults, with container rub a thin film over affected areas, not more than 3-4 times in 24 hour period, massage is not necessary.

Other information: store in cool dry place

INACTIVE INGREDIENT

Inactive Ingredients: Allantoin, Caprylic/Capric Triglyceride, Capsicum Annuum Fruit powder, Calcium Disodium EDTA, Cannabis Sativa (Aerial) Extract Oil, DL-Alpha Tocopheryl Acetate, Ethyl Alcohol, Ethylhexylglycerin, Ethylhexyl Stearate, Glycerin, Phenoxyethanol, Polysorbate 80, Propanediol, Propylene Glycol, Purified Water, Simethicone, Sodium Polyacrylate, Trideceth-6, Vitis Vinifera (Grape) seed Oil, Xanthan Gum, Beta – Caryophyllene

Feet & Legs

4% LIDOCAINE

WITH CBD 300mg